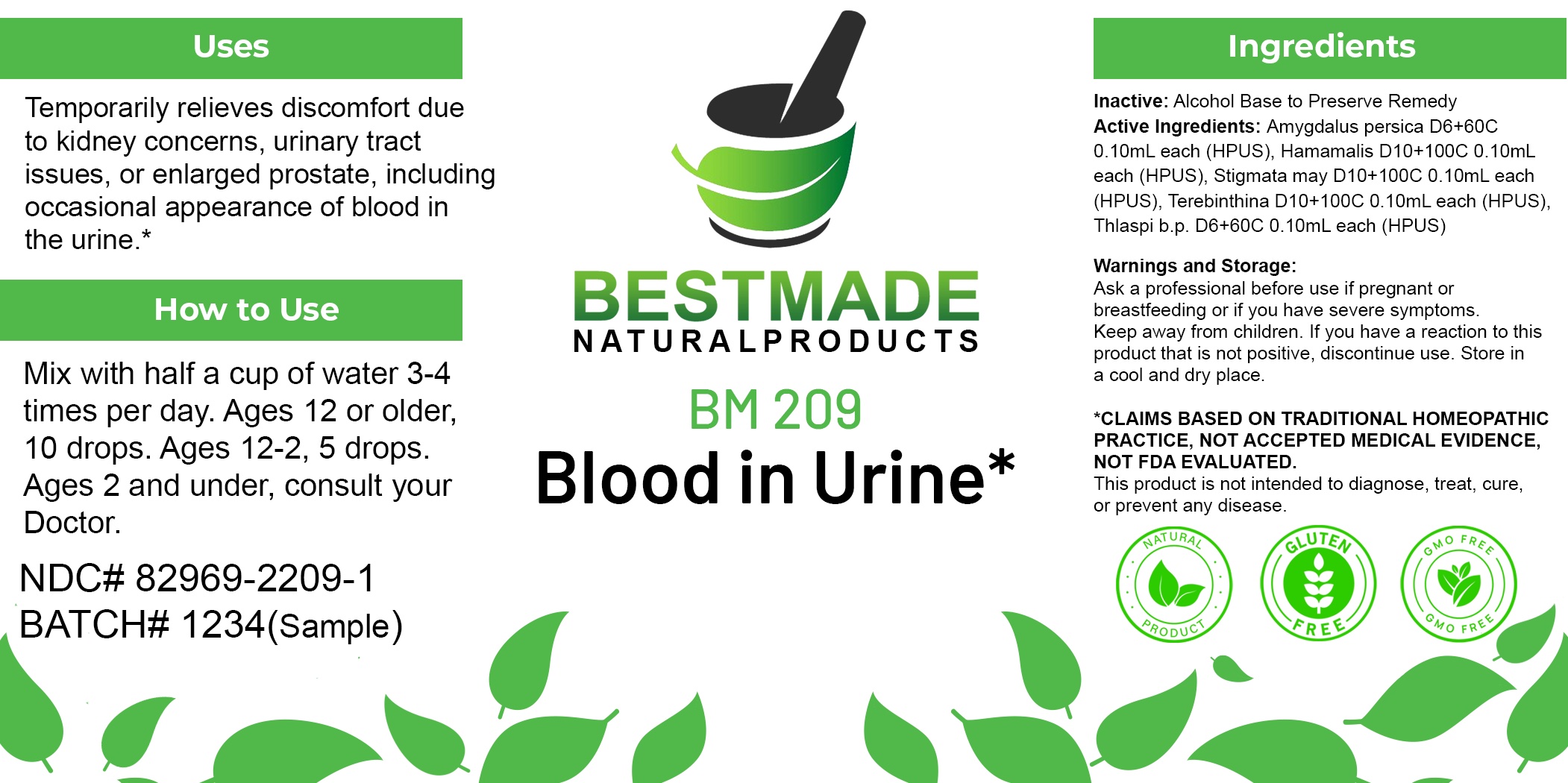 DRUG LABEL: Bestmade Natural Products BM209
NDC: 82969-2209 | Form: LIQUID
Manufacturer: Bestmade Natural Products
Category: homeopathic | Type: HUMAN OTC DRUG LABEL
Date: 20250228

ACTIVE INGREDIENTS: HAMAMELIS VIRGINIANA ROOT BARK/STEM BARK 30 [hp_C]/30 [hp_C]; TURPENTINE OIL 30 [hp_C]/30 [hp_C]; CAPSELLA BURSA-PASTORIS WHOLE 30 [hp_C]/30 [hp_C]; PEACH 30 [hp_C]/30 [hp_C]; CORN SILK 30 [hp_C]/30 [hp_C]
INACTIVE INGREDIENTS: ALCOHOL 30 [hp_C]/30 [hp_C]

BM209

DOSAGE AND ADMINISTRATION

How to Use

Mix with half a cup of water 3-4 times per day. Ages 12 or older, 10 drops. Ages 12-2, 5 drops. Ages 2 and under, consult your Doctor.

Inactive:

Alcohol Base to Preserve Product

KEEP OUT OF REACH OF CHILDREN

Warnings and Storage:

Ask a professional before use if pregnant or breastfeeding or if you have severe symptoms.

Keep away from children. If you have a reaction to this product that is not positive, discontinue use. Store in a cool and dry place

*CLAIMS BASED ON TRADITIONAL HOMEOPATHIC PRACTICE, NOT ACCEPTED MEDICAL EVIDENCE NOT FDA EVALUATED.
This product is not intended to diagnose, treat, cure, or prevent any disease.

Warnings and Storage:

Ask a professional before use if pregnant or breastfeeding or if you have severe symptoms.

Keep away from children. If you have a reaction to this product that is not positive, discontinue use. Store in a cool and dry place

*CLAIMS BASED ON TRADITIONAL HOMEOPATHIC PRACTICE, NOT ACCEPTED MEDICAL EVIDENCE NOT FDA EVALUATED.
This product is not intended to diagnose, treat, cure, or prevent any disease.

ACTIVE INGREDIENTS:

Amygdalus persica D6+60C 0.10mL each (HPUS), Hamamalis D10+100C 0.10mL each (HPUS), Stigmata may D10+100C 0.10mL each (HPUS), Terebinthina D10+100C 0.10mL each (HPUS), Thlaspi b.p. D6+60C 0.10mL each (HPUS)

Uses
Temporarily relieves discomfort due to kidney concerns, urinary tract issues, or enlarged prostate, including occasional appearance of blood in the urine.*

Uses
Temporarily relieves discomfort due to kidney concerns, urinary tract issues, or enlarged prostate, including occasional appearance of blood in the urine.*

Entire package label